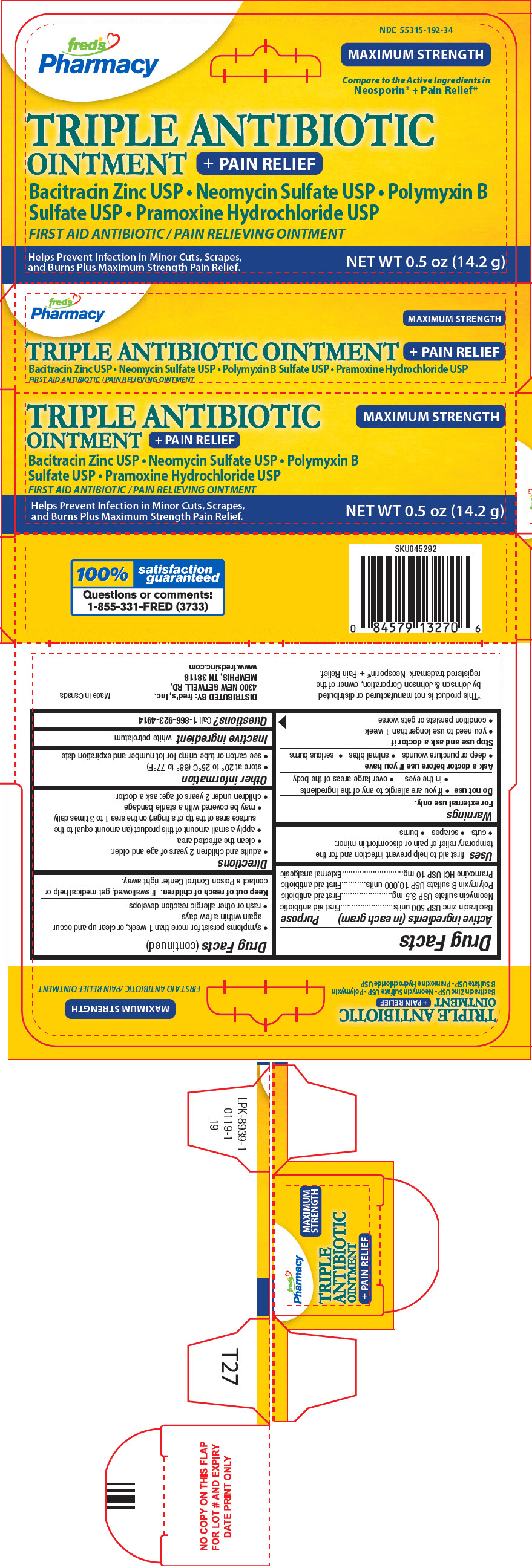 DRUG LABEL: Triple Antibiotic

NDC: 55315-192 | Form: OINTMENT
Manufacturer: FRED'S, INC.
Category: otc | Type: HUMAN OTC DRUG LABEL
Date: 20250715

ACTIVE INGREDIENTS: BACITRACIN ZINC 500 [USP'U]/1 g; NEOMYCIN SULFATE 3.5 mg/1 g; POLYMYXIN B SULFATE 10000 [USP'U]/1 g; PRAMOXINE HYDROCHLORIDE 10 mg/1 g
INACTIVE INGREDIENTS: PETROLATUM

Triple Antibiotic
Plus Pain Relief

Drug Facts

ACTIVE INGREDIENT

Active ingredients (in each gram) | Purpose
Bacitracin zinc USP 500 units | First aid antibiotic
Neomycin sulfate USP 3.5 mg | First aid antibiotic
Polymyxin B sulfate USP 10,000 units | First aid antibiotic
Pramoxine HCl USP 10 mg | External analgesic

Uses

first aid to help prevent infection and for the temporary relief of pain or discomfort in minor:

- cuts
- scrapes
- burns

Warnings

For external use only.

Do not use

- if you are allergic to any of the ingredients
- in the eyes
- over large areas of the body

Ask a doctor before use if you have

- deep or puncture wounds
- animal bites
- serious burns

Stop use and ask a doctor if

- you need to use longer than 1 week
- condition persists or gets worse
- symptoms persist for more than 1 week, or clear up and occur again within a few days
- rash or other allergic reaction develops

Keep out of reach of children.If swallowed, get medical help or contact a Poison Control Center right away.

Directions

- adults and children 2 years of age and older:
  - clean the affected area
  - apply a small amount of this product (an amount equal to the surface area of the tip of a finger) on the area 1 to 3 times daily
  - may be covered with a sterile bandage
- children under 2 years of age: ask a doctor

Other information

- store at 20° to 25°C (68° to 77°F)
- see carton or tube crimp for lot number and expiration date

Inactive ingredient

white petrolatum

Questions?

Call 1-866-923-4914

DISTRIBUTED BY: fred's, Inc.
4300 NEW GETWELL RD,
MEMPHIS, TN 38118

PRINCIPAL DISPLAY PANEL - 14.2 g Tube Carton

TRIPLE ANTIBIOTIC
OINTMENT
+ PAIN RELIEF

MAXIMUM STRENGTH

Bacitracin Zinc USP • Neomycin Sulfate USP • Polymyxin B
Sulfate USP • Pramoxine Hydrochloride USP
FIRST AID ANTIBIOTIC / PAIN RELIEVING OINTMENT

Helps Prevent Infection in Minor Cuts, Scrapes,
and Burns Plus Maximum Strength Pain Relief.

NET WT 0.5 oz (14.2 g)